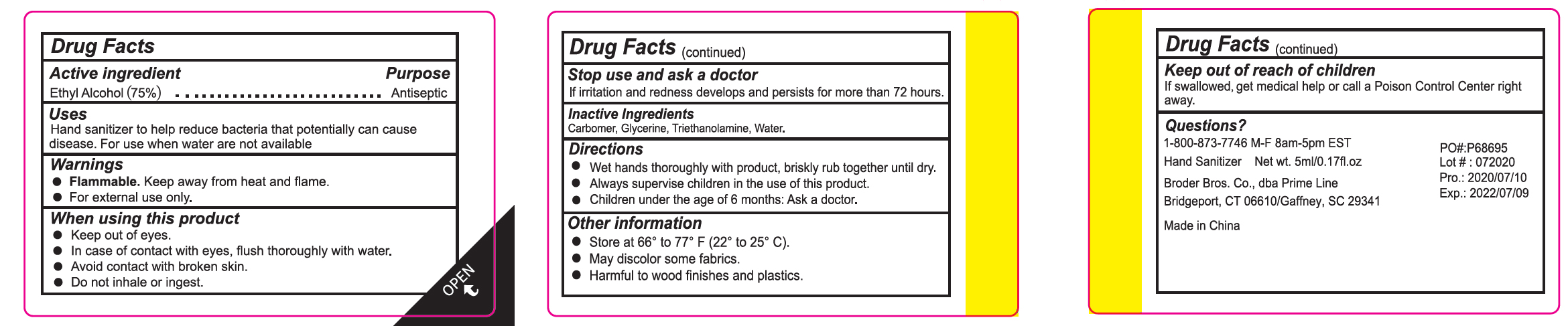 DRUG LABEL: Hand Sanitizer
NDC: 80017-001 | Form: GEL
Manufacturer: Broder Bros Prime Line
Category: otc | Type: HUMAN OTC DRUG LABEL
Date: 20200806

ACTIVE INGREDIENTS: ALCOHOL 75 mL/100 mL
INACTIVE INGREDIENTS: CARBOMER HOMOPOLYMER, UNSPECIFIED TYPE; TROLAMINE; WATER; GLYCERIN

Hand Sanitizer Gel

ACTIVE INGREDIENT

Alcohol 75% v/v. Purpose: Antiseptic

PURPOSE

Antiseptic, Hand Sanitizer

Uses

Hand sanitizer to help reduce bacteria that potentially can cause disease. For use when water are not available.

WARNINGS

Flammable, keep away from fire and flame

For external use only

When using this product

Keep out of eyes

In case of contact with eyes, flush thoroughly with water.

Avoid contact with broken skin.

Do not inhale or ingest.

Stop use and ask a doctor if irritation and redness develops and persists for more than 72 hours.

INACTIVE INGREDIENT

Water, Glycerin, Triethanolamine, Carbomer

Directions

Wet hands thoroughly with product, brisky rub together until dry.

Always supervise children in the use of this product.

Children under the age of 6 months: Ask a doctor.

OTHER SAFETY INFORMATION

Store at 66 to 77 F (22 to 25 C)

May discolor some fabrics

Harmful to wood finishes and platics

KEEP OUT OF REACH OF CHILDREN

Keep our of reach of Children. If swallowed, get medical help or call a Poison Control Center right away.

Package Label - Principal Display Panel

5 mL NDC: 80017-001-01